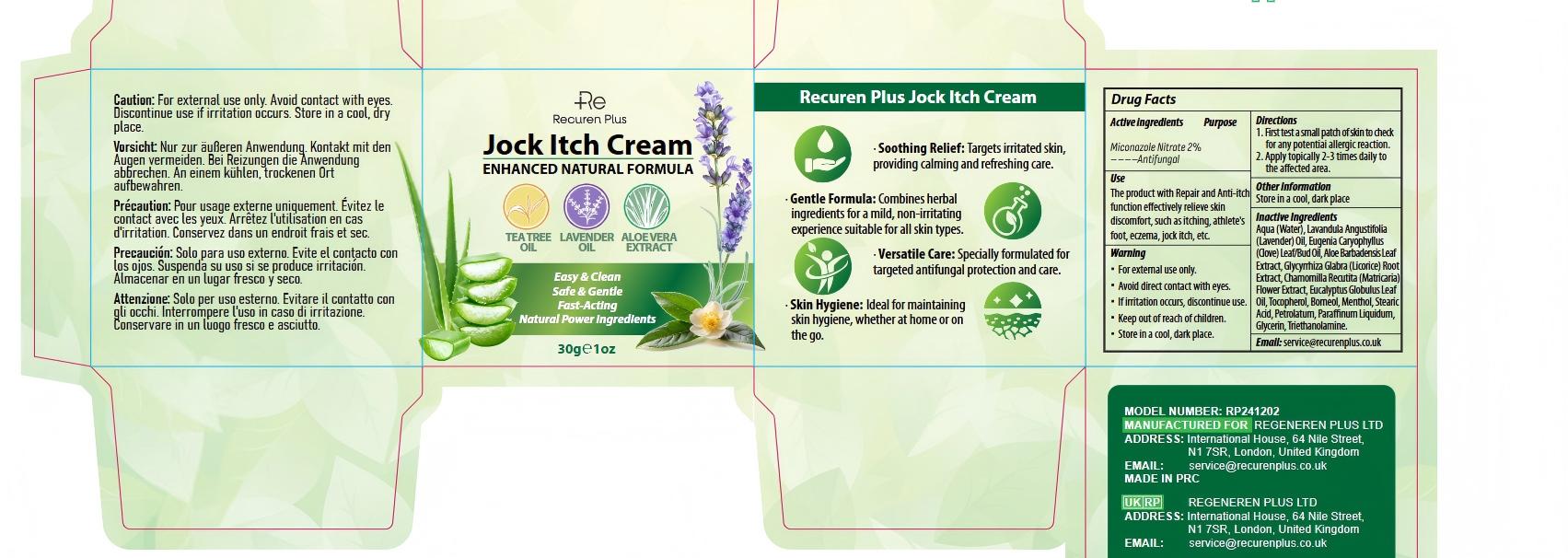 DRUG LABEL: Recuren Plus Jock Itch Cream
NDC: 87014-004 | Form: CREAM
Manufacturer: REGENEREN PLUS LTD
Category: otc | Type: HUMAN OTC DRUG LABEL
Date: 20260212

ACTIVE INGREDIENTS: MICONAZOLE NITRATE 20 mg/1 g
INACTIVE INGREDIENTS: AQUA; MENTHOL; EUCALYPTUS GLOBULUS LEAF OIL; EUGENIA CARYOPHYLLUS (CLOVE) LEAF OIL; EUGENIA CARYOPHYLLUS (CLOVE) BUD OIL; BORNEOL; PETROLATUM; TRIETHANOLAMINE; LAVANDULA ANGUSTIFOLIA (LAVENDER) OIL; MATRICARIA CHAMOMILLA WHOLE; ALOE BARBADENSIS LEAF; GLYCYRRHIZA GLABRA (LICORICE) ROOT; PARAFFINUM LIQUIDUM; GLYCERIN; TOCOPHEROL; STEARIC ACID

ACTIVE INGREDIENT

MICONAZOLE NITRATE 2%

PURPOSE

Antifungal

INDICATIONS AND USAGE

For the effective treatment of jock itch (tinea cruris), athlete’s foot (tinea pedis), ringworm (tinea corporis), and other common fungal skin infections.

WARNINGS

For external use only

DO NOT USE

On children under 3 years of age

OTHER SAFETY INFORMATION

Store in a cool, dry place

STOP USE

Irritation occurs or if there is no improvement within 4 weeks.

KEEP OUT OF REACH OF CHILDREN

If swallowed, get medical help immediately.

WHEN USING

Avoid contact with the eyes

ASK DOCTOR

You have concerns about skin irritation or if symptoms persist beyond 4 weeks.

DOSAGE AND ADMINISTRATION

1. Apply a small amount of cream to the affected area 2–3 times daily. 2. Make sure the skin is clean and dry before application. 3. For first-time users, perform a patch test on a small area of skin to check for sensitivity.

INACTIVE INGREDIENT

Aqua (Water), Lavandula Angustifolia (Lavender) Oil, Eugenia Caryophyllus (Clove) Leaf/Bud Oil, Aloe Barbadensis Leaf Extract, Glycyrrhiza Glabra (Licorice) Root Extract, Chamomilla Recutita (Matricaria) Flower Extract, Eucalyptus Globulus Leaf Oil, Tocopherol, Borneol, Menthol, Stearic Acid, Petrolatum, Paraffinum Liquidum, Glycerin, Triethanolamine.

QUESTIONS

Please contact the email: service@recurenplus.co.uk